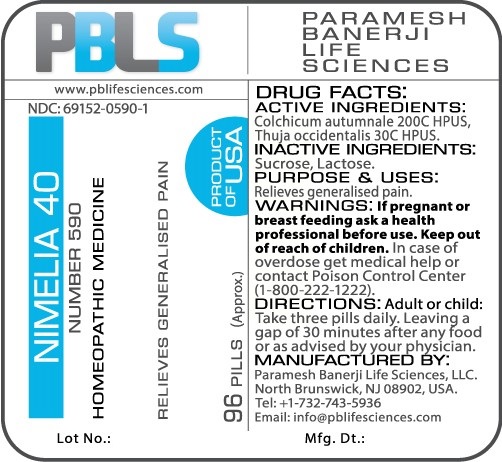 DRUG LABEL: Nimelia 40 Number 590
NDC: 69152-0590 | Form: PELLET
Manufacturer: Paramesh Banerji Life Sciences LLC
Category: homeopathic | Type: HUMAN OTC DRUG LABEL
Date: 20170215

ACTIVE INGREDIENTS: THUJA OCCIDENTALIS LEAFY TWIG 30 [hp_C]/1 1; COLCHICUM AUTUMNALE BULB 200 [hp_C]/1 1
INACTIVE INGREDIENTS: LACTOSE; SUCROSE

DRUG FACTS: Active Ingredients

Colchicum autumnale 200C HPUS, Thuja occidentalis 30C HPUS

Inactive Ingredients

Sucrose, Lactose

Purpose

Relieves generalized pain

Uses

Relieves generalized pain

Warnings

If pregnant or breast feeding ask a health professional before use.

Keep out of reach of children. In case of overdose, get medical help or contact a Poison Control Center (1-800-222-1222) right away.

Direction

Adult or child: Take three pills daily. Leaving a gap of 30 minutes after any food or as advised by your physician.

Manufactured by

Paramesh Banerji Life Sciences, LLC.

North Brunswick, NJ 08902, USA.

Tel: +1-732-743-5936

Email: info@pblifesciences.com

Principal Display Panel

NDC: 69152-0590-1

Nimelia 40

Number 590

Homeopathic Medicine

Relieves generalized pain

96 Pills (Approx.)

Product of USA